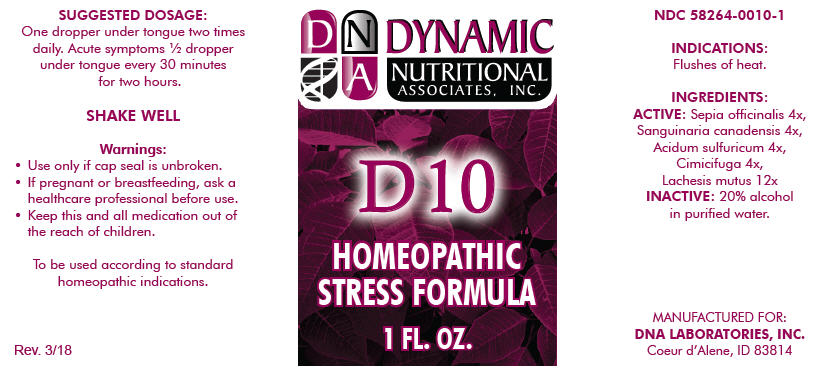 DRUG LABEL: D-10
NDC: 58264-0010 | Form: SOLUTION
Manufacturer: DNA Labs, Inc.
Category: homeopathic | Type: HUMAN OTC DRUG LABEL
Date: 20250113

ACTIVE INGREDIENTS: SEPIA OFFICINALIS WHOLE 4 [hp_X]/1 mL; SANGUINARIA CANADENSIS ROOT 4 [hp_X]/1 mL; SULFURIC ACID 4 [hp_X]/1 mL; BLACK COHOSH 4 [hp_X]/1 mL; LACHESIS MUTA VENOM 12 [hp_X]/1 mL
INACTIVE INGREDIENTS: ALCOHOL; WATER

D-10

NDC 58264-0010-1

INDICATIONS

PURPOSE

Flushes of heat.

INGREDIENTS

ACTIVE

Sepia officinalis 4x, Sanguinaria canadensis 4x, Acidum sulfuricum 4x, Cimicifuga 4x, Lachesis mutus 12x

INACTIVE

20% alcohol in purified water.

SUGGESTED DOSAGE

One dropper under tongue two times daily. Acute symptoms ½ dropper under tongue every 30 minutes for two hours.

STORAGE AND HANDLING

SHAKE WELL

Warnings

- Use only if cap seal is unbroken.

PREGNANCY OR BREAST FEEDING

- If pregnant or breastfeeding, ask a healthcare professional before use.

KEEP OUT OF REACH OF CHILDREN

- Keep this and all medication out of the reach of children.

To be used according to standard homeopathic indications.

PRINCIPAL DISPLAY PANEL - 1 FL. OZ. Bottle Label

DYNAMIC
NUTRITIONAL
ASSOCIATES, INC.

D 10

HOMEOPATHIC
STRESS FORMULA

1 FL. OZ.